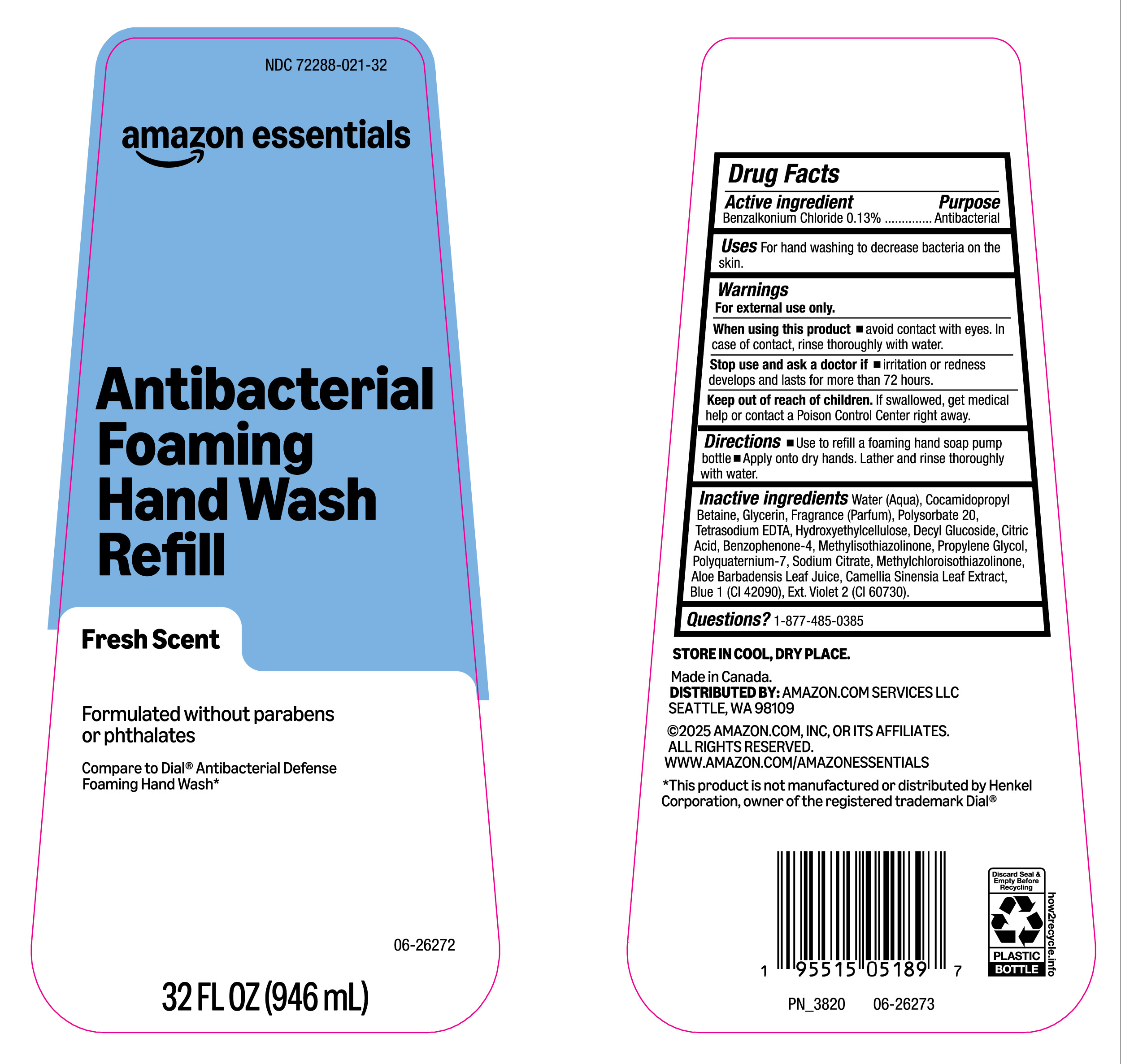 DRUG LABEL: Benzalkonium Chloride
NDC: 72288-021 | Form: LIQUID
Manufacturer: AMAZON.COM SERVICES LLC
Category: otc | Type: HUMAN OTC DRUG LABEL
Date: 20251002

ACTIVE INGREDIENTS: BENZALKONIUM CHLORIDE 130 mg/100 mL
INACTIVE INGREDIENTS: METHYLCHLOROISOTHIAZOLINONE; POLYQUATERNIUM-7; SODIUM CITRATE; BLUE 1; CAMELLIA SINENSIS LEAF; EXT. VIOLET 2; GLYCERIN; POLYSORBATE 20; WATER; BENZOPHENONE-4; FRAGRANCE CLEAN ORC0600327; ALOE BARBADENSIS LEAF JUICE; CITRIC ACID; METHYLISOTHIAZOLINONE; TETRASODIUM EDTA; COCAMIDOPROPYL BETAINE; PROPYLENE GLYCOL; HYDROXYETHYLCELLULOSE; DECYL GLUCOSIDE

NDC 72288-021, Amazon essentials.

Active Ingredient

Benzalkonium Chloride (0.13%)

Purpose

Antibacterial.

Uses

For hand washing to decrease bacteria on the skin.

Warnings

For external use only.

When using this product

- Avoid contact with eyes. In case of contact, rinse throughly with water.

Stop use and ask a doctor if

- Irritaion or redness develops and lasts for more than 72 hours.

Keep out of reach of children.

If swallowed, get medical help or contact a Poison Control Center right awsy.

Directions

- Use to refil a foaming hand soap pump bottle.
- Apply onto dry hands. Lather and rinse thoroghly with water,

Inactive Ingredients.

Water (Aqua), Cocamidopropyl Betaine, Glycerin, Fragrance (Parfum), Polysorbate 20, Tetrasodium EDTA, Hydroxyethylcellulose, Decyl Glucoside, Citric Acid, Benzophenone-4, Methylisothiazolinone, Propylene Glycol, Polyquaternium-7, Sodium Citrate, Methylchloroisothiazolinone, Aloe Barbadensis Leaf Juice, Camellia Sinensia Leaf Extract, Blue 1 (CI 42090), Ext.Violet 2 (CI 60730).

Questions?

1-877-485-0385